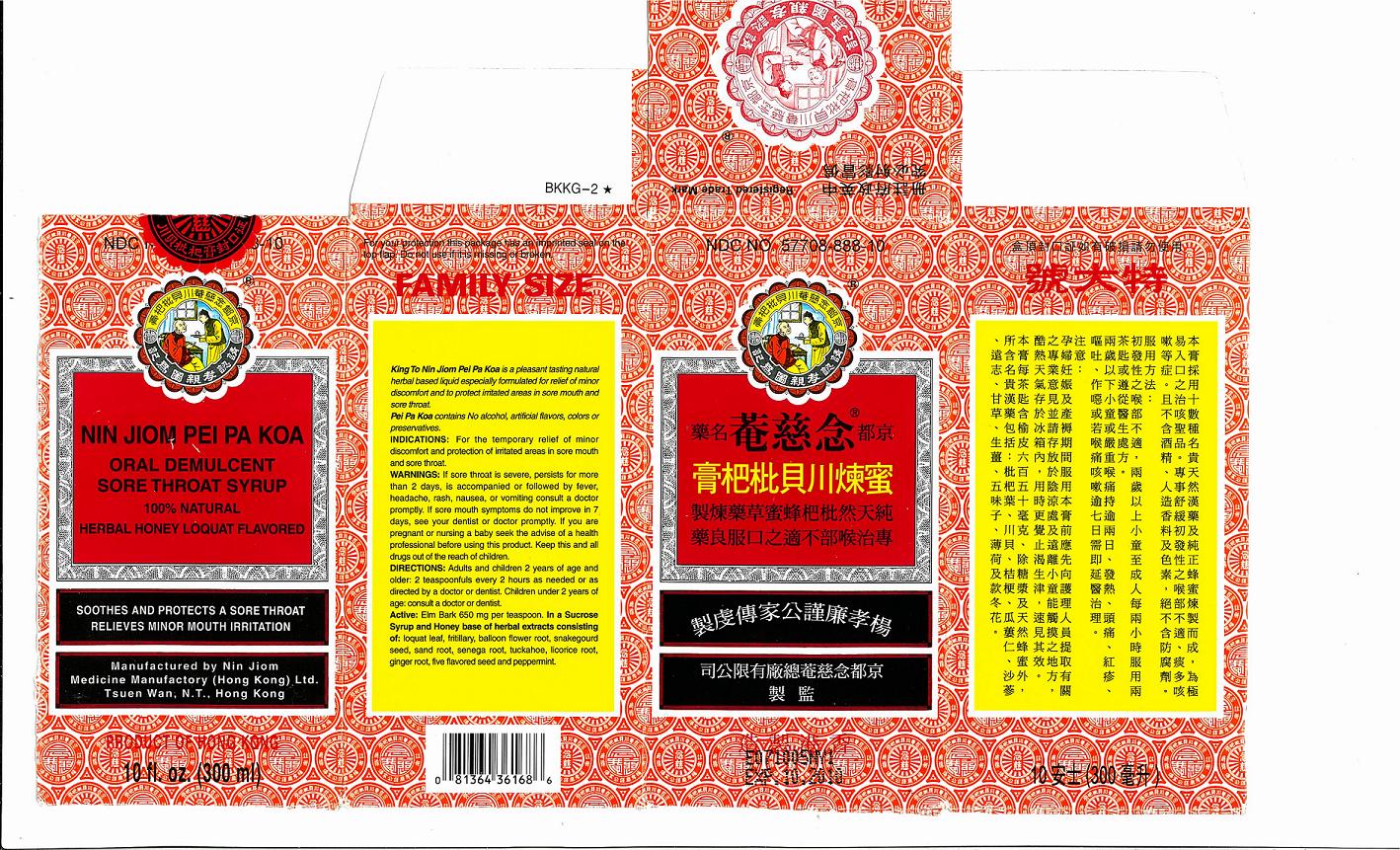 DRUG LABEL: NIN JIOM PEI PA KOA
NDC: 57708-888 | Form: SYRUP
Manufacturer: NIN JIOM MEDICINE MANUFACTORY (HK) LTD
Category: otc | Type: HUMAN OTC DRUG LABEL
Date: 20110310

ACTIVE INGREDIENTS: ELM 650 mg/5 mL
INACTIVE INGREDIENTS: SUCROSE; PLATYCODON GRANDIFLORUM LEAF; FRITILLARIA PRZEWALSKII BULB; ERIOBOTRYA JAPONICA LEAF; GLEHNIA LITTORALIS ROOT; HONEY; POLYGALA SENEGA ROOT; GREATER GALANGAL; LICORICE; GINGER; PEPPERMINT; FU LING; SCHISANDRA CHINENSIS FRUIT; TRICHOSANTHES CUCUMERINA SEED

Product Facts

DESCRIPTION

King to Nin Jiom Pei Pa Koa is a pleasant tasting natural herbal based liquid especially formulated for relief of minor discomfort and to protect irritated areas in sore mouth and sore throat.

Pei Pa Koa contains No Alcohol, artificial flavors, colors, or preservatives.

INDICATIONS

For the temporary relief of minor discomfort and protection of irritated areas in sore mouth and sore throat.

DIRECTIONS:

Adults and Children 2 years of age and older: 2 teaspoonfuls every 2 hours as needed or as directed by a doctor or dentist.
Children under 2 years of age: Consult a doctor or dentist.

WARNINGS

If sore throat is severe, persists for more than 2 days, is accompanied or followed by fever, headache, rash, nausea, or vomiting consult a doctor promptly. If sore mouth symptoms do not improve in 7 days, see your dentist or doctor promptly. If you are pregnant or nursing a baby seek the advice of a health professional before using this product. Keep this and all drugs out of the reach of children.

KEEP OUT OF REACH OF CHILDREN

Keep this and all drugs out of the reach of children.

Active:

Elm Bark 650 mg per teaspoon.

In a Sucrose Syrup and Honey base of herbal extracts consisting of:

loquat leaf, fritillary, balloon flower root, snakegourd seed, sand root, senega root, tuckahoe, licorice root, ginger root, five flavored seed, and peppermint.

PURPOSE

For the temporary relief of minor discomfort and protection of irritated areas in sore mouth and sore throat.